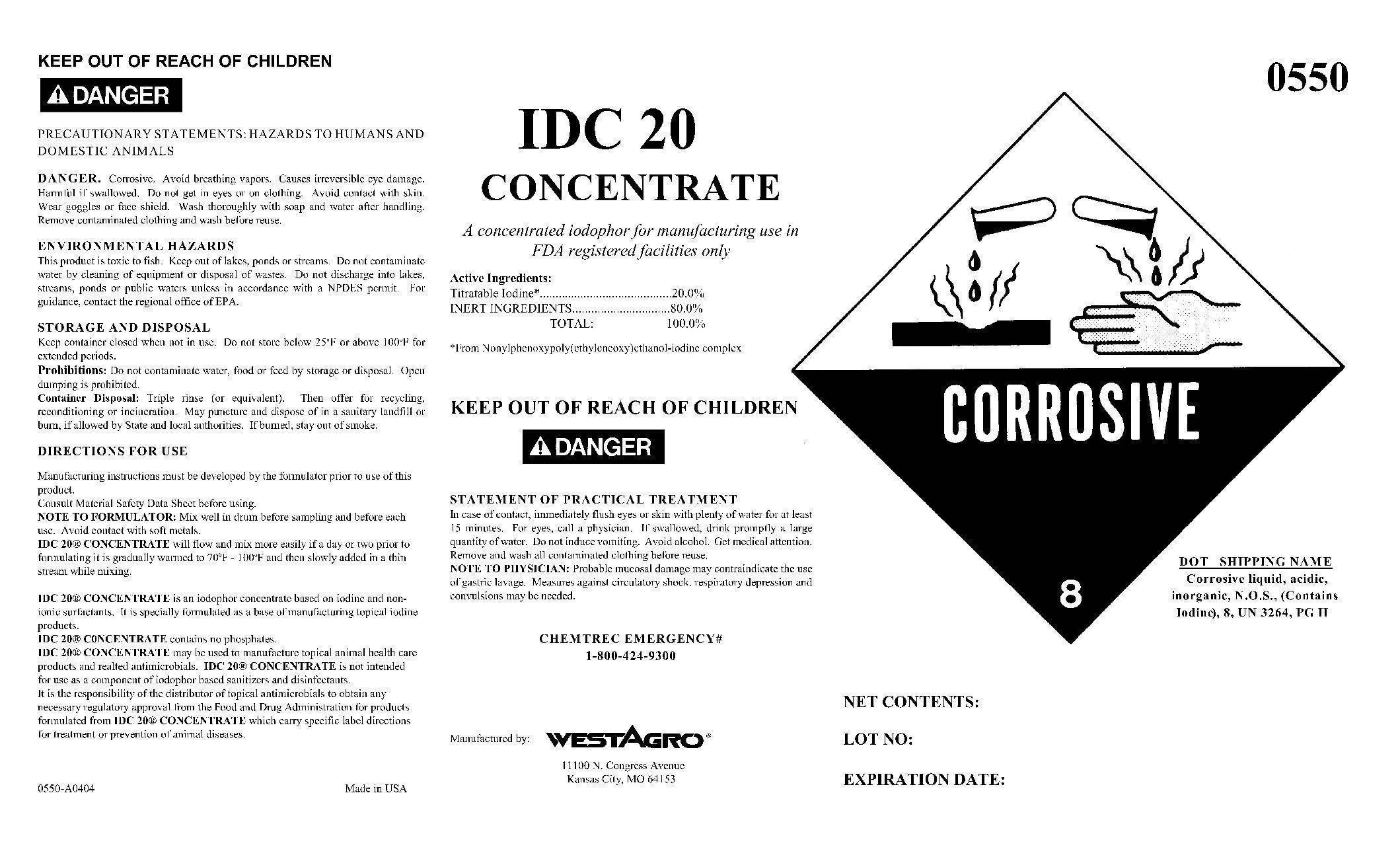 DRUG LABEL: IDC 20 Concentrate
NDC: 33392-550 | Form: SOLUTION, CONCENTRATE
Manufacturer: WestAgro, Inc.
Category: animal | Type: OTC ANIMAL DRUG LABEL
Date: 20211215

ACTIVE INGREDIENTS: Iodine 200 g/1 kg

IDC 20 CONCENTRATE

A concentrated iodophor for manufacturing use in FDA registered facilities only

Active Ingredients:
Titratable Iodine ................................................ 20.0%
INERT INGREDIENTS ......................................... 80.0%
TOTAL: .............. 100.0%

From Nonylphenoxypoly(ethyleneoxy)ethanol-iodine complex

KEEP OUT OF REACH OF CHILDREN

! DANGER

STATEMENT OF PRACTICAL TREATMENT

In case of contact, immediately flush eyes or skin with plenty of water for at least 15 minutes. For eyes, call a physician. If swallowed, drink promptly a large quantity of water. Do not induce vomiting. Avoid alcohol. Get medical attention. Remove and wash all contaminated clothing before reuse.

NOTE TO PHYSICIAN: Probable mucosal damage may contraindicate the use of gastric lavage. Measures against circulatory shock, respiratory depression and convulsions may be needed.

Chemtrec Emergency No.

1-800-424-9300

Manufactured by: WESTAGRO
11100 N. Congress Avenue
Kansas City, MO 64153

KEEP OUT OF REACH OF CHILDREN

! DANGER

WARNINGS AND PRECAUTIONS

PRECAUTIONARY STATEMENTS: HAZARDS TO HUMANS AND DOMESTIC ANIMALS

DANGER. Corrosive. Avoid breathing vapors. Causes irreversible eye damage. Harmful if swallowed. Do not get in eyes or on clothing. Avoid contact with skin. Wear goggles or face shield. Wash thoroughly with soap and water after handling. Remove contaminated clothing and wash before reuse.

ENVIRONMENTAL HAZARDS

This product is toxic to fish. Keep out of lakes, ponds or streams. Do not contaminate water by cleaning of equipment or disposal of wastes. Do not discharge into lakes, streams, ponds or public waters unless in accordance with a NPDES permit. For guidance, contact the regional office of EPA.

STORAGE AND DISPOSAL

Keep container closed when not in use. Do not store below 25 deg F or above 100 deg F for extended periods.

Prohibitions: Do not contaminate water, food or feed by storage or disposal. Open dumping is prohibited.

Container Disposal: Triple rinse (or equivalent). Then offer for recycling, reconditioning or incineration. May puncture and dispose of in a sanitary landfill or burn, if allowed by State and local authorities. If burned, stay out of smoke.

INDICATIONS AND USAGE

DIRECTIONS FOR USE

Manufacturing instructions must be developed by the formulator prior to use of this product.
Consult Material Safety Data Sheet before using.
NOTE TO FORMULATOR: Mix well in drum before sampling and before each use. Avoid contact with soft metals.
IDC 20 CONCENTRATE will flow and mix more easily if a day or two prior to formulating it is gradually warmed to 70 deg F - 100 deg F and then slowly added in a thin stream while mixing.

IDC 20 CONCENTRATE is an iodophor concentrate based on iodine and non-ionic surfactants. It is specially formulated as a base of manufacturing topical iodine products.
IDC 20 CONCENTRATE contains no phosphates.
IDC 20 CONCENTRATE may be used to manufacture topical animal health care products and related antimicrobials. IDC 20 CONCENTRATE is not intended for use as a component of iodophor based sanitizers and disinfectants.
It is the responsibility of the distributor of topical antimicrobials to obtain any necessary regulatory approval from the Food and Drug Administration for products formulated from IDC 20 CONCENTRATE which carry specific label directions for treatment or prevention of animal diseases.

0550-A0404 Made in U.S.A.

0550

CORROSIVE

8

DOT SHIPPING NAME
Corrosive liquid, acidic,
inorganic, N.O.S., (Contains
Iodine), 8, UN 3264, PG II

NET CONTENTS:

LOT NO:

EXPIRATION DATE: